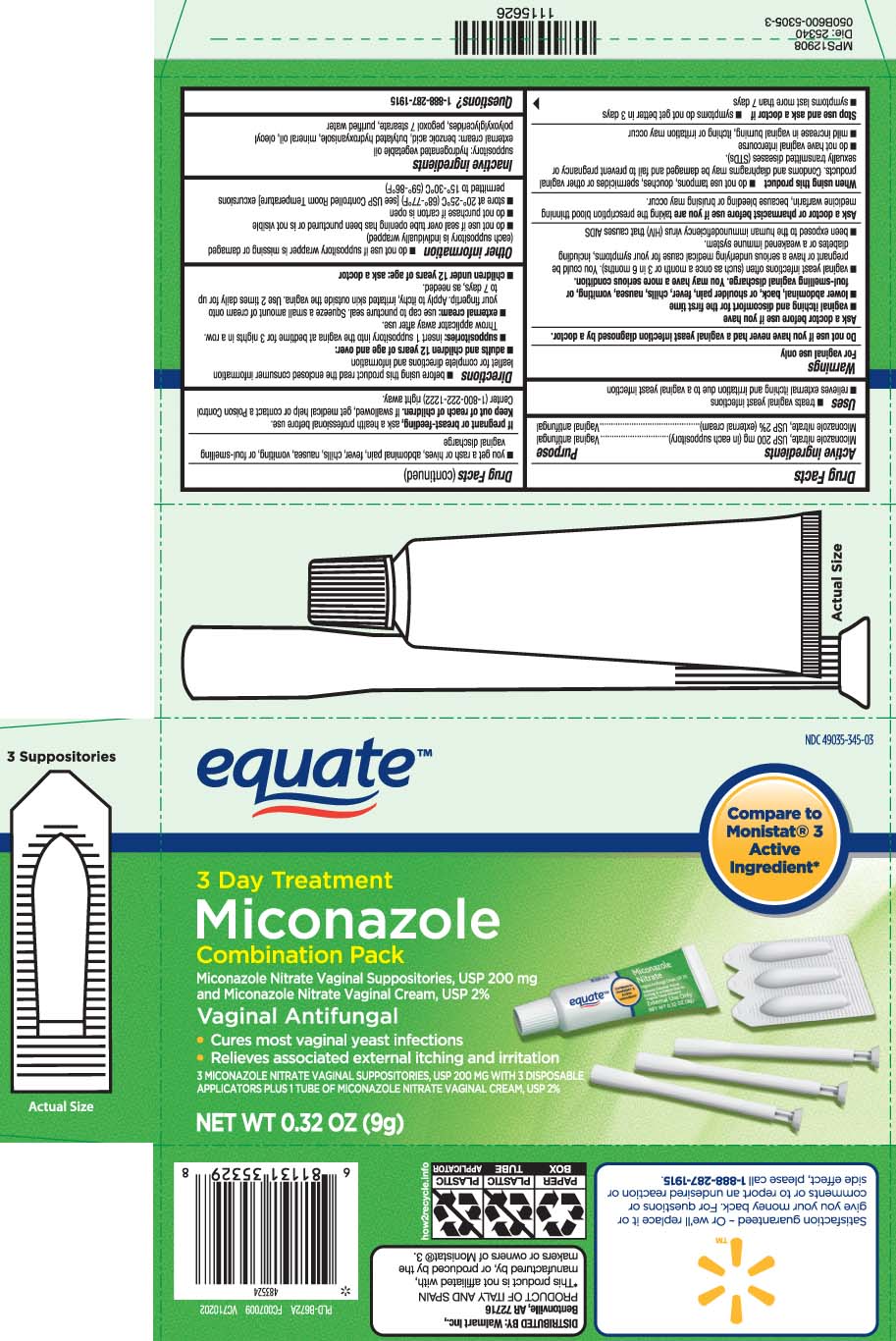 DRUG LABEL: Miconazole 3 Combination Pack
NDC: 49035-345 | Form: KIT | Route: VAGINAL
Manufacturer: EQUATE (Wal-Mart Stores, Inc.) (see also WAL-MART INC)
Category: otc | Type: HUMAN OTC DRUG LABEL
Date: 20250908

ACTIVE INGREDIENTS: MICONAZOLE NITRATE 200 mg/1 1; MICONAZOLE NITRATE 10 mg/0.5 g
INACTIVE INGREDIENTS: HYDROGENATED PALM KERNEL OIL; BENZOIC ACID; BUTYLATED HYDROXYANISOLE; MINERAL OIL; APRICOT KERNEL OIL PEG-6 ESTERS; PEGOXOL 7 STEARATE; WATER

Miconazole 3 Combination Pack

Active ingredients

Miconazole nitrate, USP 200 mg (in each suppository)
Miconazole nitrate, USP 2% (external cream)

Purpose

Vaginal antifungal

Vaginal antifungal

Uses

- treats vaginal yeast infections
- relieves external itching and irritation due to a vaginal yeast infection

Warnings

For vaginal use only

Do not use

if you have never had a vaginal yeast infection diagnosed by a doctor.

Ask a doctor before use if you have

- vaginal itching and discomfort for the first time
- lower abdominal, back or shoulder pain, fever, chills, nausea, vomiting, or foul-smelling vaginal discharge. You may have a more serious condition.
- vaginal yeast infections often (such as once a month or 3 in 6 months). You could be pregnant or have a serious underlying medical cause for your symptoms, including diabetes or a weakened immune system.
- been exposed to the human immunodeficiency virus (HIV) that causes AIDS

Ask a doctor or pharmacist before use if you are

taking the prescription blood thinning medicine warfarin, because bleeding or bruising may occur

When using this product

- do not use tampons, douches, spermicides or other vaginal products. Condoms and diaphragms may be damaged and fail to prevent pregnancy or sexually transmitted diseases (STDs)
- do not have vaginal intercourse
- mild increase in vaginal burning, itching or irritation may occur

Stop use and ask a doctor if

- symptoms do not get better in 3 days
- symptoms last more than 7 days
- you get a rash or hives, abdominal pain, fever, chills, nausea, vomiting, or foul-smelling vaginal discharge

If pregnant or breast-feeding,

ask a health professional before use.

Keep out of reach of children.

If swallowed, get medical help or contact a Poison Control Center right away.

Directions

- before using this product read the enclosed consumer information leaflet for complete directions and information
- adults and children 12 years of age and over:
  - suppositories: insert 1 suppository into the vagina at bedtime for 3 nights in a row. Wash applicator away after use.
  - external cream: Use cap to puncture seal. Squeeze a small amount of cream onto your fingertip. Gently apply the cream onto the itchy, irritated skin outside the vagina. Use 2 times daily for up to 7 days, as needed.
- children under 12 years of age: ask a doctor

Other information

- do not use if suppository wrapper is missing or damaged (each suppository is individually wrapped)
- do not use if seal over tube opening has been punctured or is not visible
- do not purchase if carton is open
- store at 20º - 25ºC (68º - 77ºF) [see USP controlled Room Temperature] excursions permitted to 15°-30°C (59°-86°F)

Inactive ingredients

- suppository: hydrogenated vegetable oil
- external cream: benzoic acid, butylated hydroxyanisole, mineral oil, oleoyl polyoxylglycerides, pegoxol 7 stearate, purified water

Questions?

1-888-287-1915

Principal Display Panel

Compare to Monistat® 3 active ingredient*

3 Day Treatment

Miconazole

Combination Pack

Vaginal antifungal

Miconazole nitrate vaginal suppositories, USP 200 mg

and Miconazole nitrate vaginal cream, USP 2%

Vaginal Antifungal

- Cures most vaginal yeast infections
- Relieves associated external itching and irritation

3 miconazole nitrate vaginal suppositories, USP 200 mg with 1 reusable applicator plus

1 tube of miconazole nitrate vaginal cream, USP 2%

Net wt. oz (g)

*This product is not affiliated with, manufactured by, or produced by the makers or owners of Monistat® 3.

Distributed by:

Wal-Mart Inc

Bentonville AR 72716

Package Label

EQUATE Miconazole 3 Day Combination Pack Treatment